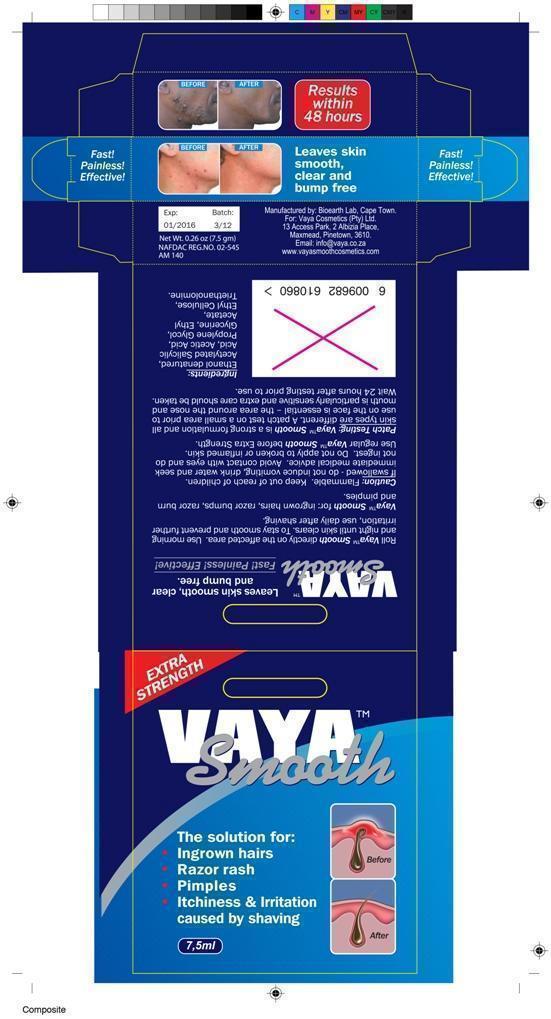 DRUG LABEL: Vaya Smooth Male
NDC: 62955
Manufacturer: Vaya Smooth Cosmetics (Pty) Ltd
Category: other | Type: COSMETIC
Date: 20141029

Vaya Smooth Aftershave

5981bc8e-271b-438d-b8c2-0f1122c84f54.jpg vaya smooth packaging label male

5981bc8e-271b-438d-b8c2-0f1122c84f54.jpg

vaya smooth packaging label male0.75ml